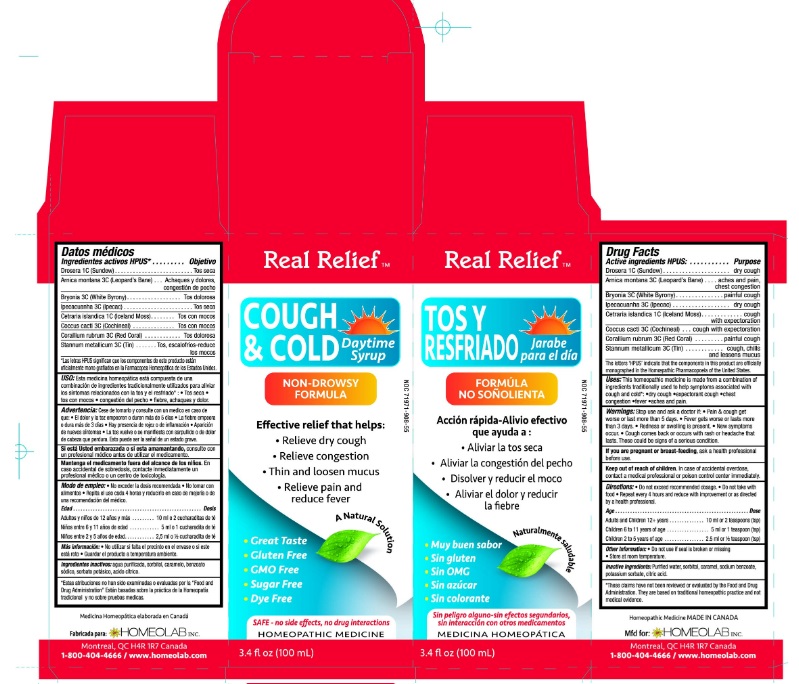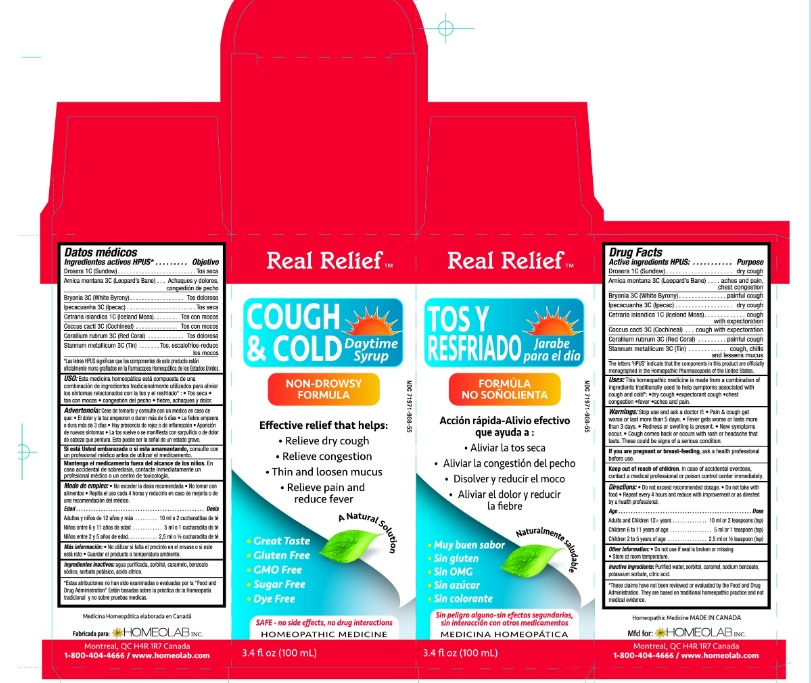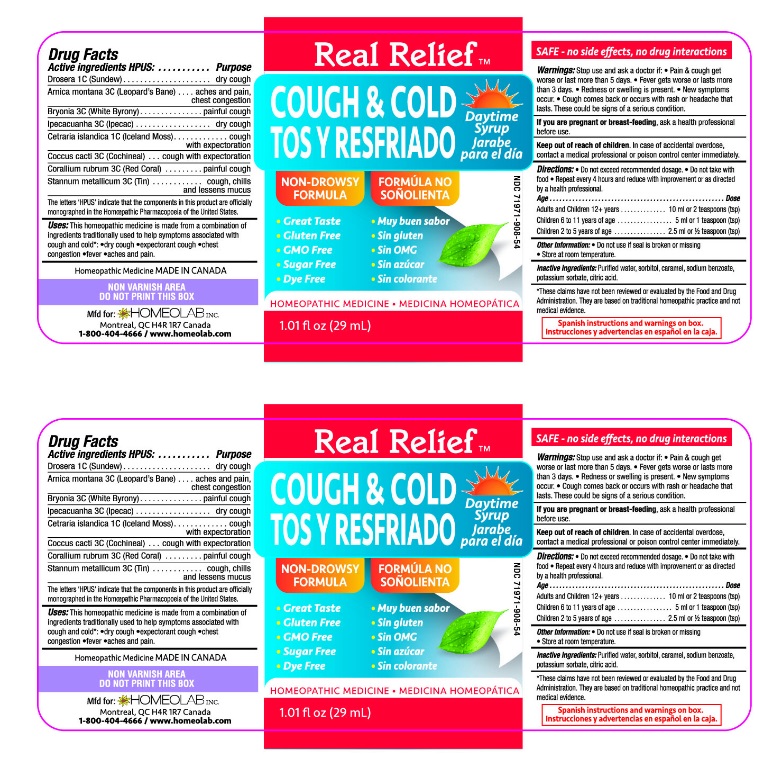 DRUG LABEL: Real Relief
NDC: 63388-918 | Form: LIQUID
Manufacturer: Laboratoire Atlas Inc
Category: homeopathic | Type: HUMAN OTC DRUG LABEL
Date: 20251008

ACTIVE INGREDIENTS: DROSERA ROTUNDIFOLIA FLOWERING TOP 1 [hp_C]/100 mL; ARNICA MONTANA 3 [hp_C]/100 mL; BRYONIA ALBA WHOLE 3 [hp_C]/100 mL; IPECAC 3 [hp_C]/100 mL; CETRARIA ISLANDICA SUBSP. ISLANDICA 1 [hp_C]/100 mL; PROTORTONIA CACTI 3 [hp_C]/100 mL; CORALLIUM RUBRUM WHOLE 3 [hp_C]/100 mL; TIN 3 [hp_C]/100 mL
INACTIVE INGREDIENTS: WATER; SORBITOL; CARAMEL; SODIUM BENZOATE; POTASSIUM SORBATE; CITRIC ACID MONOHYDRATE

Active Ingredients HPUS:

Drosera 1C (Sundew)

Arnica montana 3C (Leopard's Bane)

Bryonia 3C (White Bryony)

Ipecacuanha 3C (Ipecac)

Cetraria islandica 1C (Iceland Moss)

Coccus cacti 3C (Cochineal)

Corallium rubrum 3C (Red Coral)

Stannum metallicum 3C (Tin)

The letters "HPUS" indicate that the components in this product are officially

monographed in the Homeopathic Pharmacopoeia of the United States

Purpose

Drosera 1C (Sundew)...............................................dry cough

Arnica montana 3C (Leopard's Bane)..........................aches and pains, chest congestion

Bryonia 3C (White Bryony).......................................painful cough

Ipecacuanha 3C (Ipecac).........................................dry cough

Cetraria islandica 1C (Iceland Moss)..........................cough with expectoration

Coccus cacti 3C (Cochineal).....................................cough with expectoration

Corallium rubrum 3C (Red Coral)..............................painful cough

Stannum metallicum 3C (Tin)..................................coughs, chills and lessens mucus

INDICATIONS AND USAGE

Uses: This homeopathic medicine is made from a combination of

ingredients traditionally used to help symptoms assiciated with

cough and cold* •dry cough •expectorant cough •chest

congestion •fever •aches and pains

WARNINGS

Warnings: Stop use and ask a doctor if: •Pain & cough get

worse or last more than 5 days. •Fever gets worse or lasts more

than 3 days •Redness or swelling is present •New symptoms

occur •Cough comes back or occurs with a rash or headache that

lasts. These could be signs of a serious condition.

If you are pregnant or breast-feeding, ask a health professional

before use.

Keep out of reach of children. In case of accidental overdose,

contact a medical professional or poison control center immediately.

DOSAGE AND ADMINISTRATION

Directions: •Do not exceed recommended dosage. •Do not take with

food •Repeat every 4 hours and reduce with improvement or as directed

by a health professional.

Age................................................................ Dose

Adults and children 12+ years...........................10 ml or 2 teaspoons (tsp)

Children 6 to 11 years of age.............................5 ml or 1 teaspoon (tsp)

Children 2 to 5 years of age...............................2.5 ml or 1/2 teaspoon (tsp)

Other information: •Do not use if seal is broken or missing

•Store at room temperature

INACTIVE INGREDIENT

Inactive Ingredients:Purified water, sorbitol, caramel, sodium benzoate,

potassium sorbate, citric acid